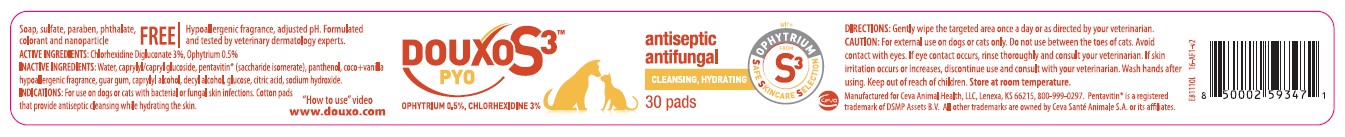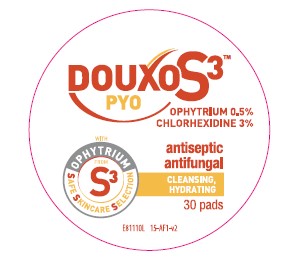 DRUG LABEL: DOUXO S3
NDC: 13744-157 | Form: SWAB
Manufacturer: Ceva Sante Animale
Category: animal | Type: OTC ANIMAL DRUG LABEL
Date: 20250312

ACTIVE INGREDIENTS: OPHIOPOGON JAPONICUS ROOT 5.0 mg/1 1; CHLORHEXIDINE 30 mg/1 1
INACTIVE INGREDIENTS: CAPRYLYL/CAPRYL OLIGOGLUCOSIDE; SACCHARIDE ISOMERATE; GUAR GUM; CAPRYLYL GLYCOL; DECYL ALCOHOL; ANHYDROUS DEXTROSE; CITRIC ACID MONOHYDRATE; SODIUM HYDROXIDE

DOUXO S3™ PYO

OPHYTRIUM 0.5%, CHLORHEXIDINE 3%

Soap, sulfate, paraben, phthalate, colorant and nanoparticle FREE

Hypoallergenic fragrance, adjusted pH. Formulated and tested by veterinary dermatology experts.

ACTIVE INGREDIENTS: Chlorhexidine Digluconate 3%, Ophytrium 0.5%

INACTIVE INGREDIENT

INACTIVE INGREDIENTS: Water, caprylyl/capryl glucoside, pentavitin® (saccharide isomerate), panthenol, coco+vanilla hypoallergenic fragrance, guar gum, caprylyl alcohol, decyl alcohol, glucose, citric acid, sodium hydroxide.

INDICATIONS AND USAGE

INDICATIONS: For use on dogs or cats with bacterial or fungal skin infections. Cotton pads that provide antiseptic cleansing while hydrating the skin.

DIRECTIONS: Gently wipe the targeted area once a day or as directed by your veterinarian.

"How to use" video www.douxo.com

PRECAUTIONS

CAUTION: For external use on dogs or cats only. Do not apply between the toes of cats. Avoid contact with eyes. If eye contact occurs, rinse thoroughly and consult your veterinarian. If skin irritation occurs or increases, discontinue use and consult with your veterinarian. Wash hands after using. Keep out of reach of children. Store at room temperature.

Manufactured for Ceva Animal Health, LLC, Lenexa, KS 66215, 800-999-0297. Pentavitin® is a registered trademark of DSMP Assets B.V. All other trademarks are owned by Ceva Santé Animale S.A. or its affiliates.

PRINCIPAL DISPLAY PANEL - 30 Pad Jar and Lid

DOUXO S3™ PYO

OPHYTRIUM 0.5%, CHLORHEXIDINE 3%

antiseptic

antifungal

CLEANSING, HYDRATING

30 pads